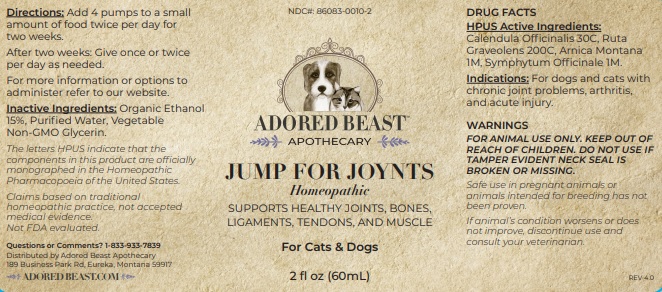 DRUG LABEL: JUMP FOR JOYNTS
NDC: 86083-0010 | Form: LIQUID
Manufacturer: The Adored Beast Apothecary, Ltd
Category: homeopathic | Type: OTC ANIMAL DRUG LABEL
Date: 20251027

ACTIVE INGREDIENTS: CALENDULA OFFICINALIS WHOLE 30 [hp_C]/60 mL; RUTA GRAVEOLENS WHOLE 200 [hp_C]/60 mL; ARNICA MONTANA WHOLE 1 [hp_M]/60 mL; COMFREY ROOT 1 [hp_M]/60 mL
INACTIVE INGREDIENTS: ALCOHOL; WATER; GLYCERIN

JUMP FOR JOYNTS

DRUG FACTS

HPUS Active Ingredients:
Calendula Officinalis 30C, Ruta
Graveolens 200C, Arnica Montana
1M, Symphytum Officinale 1M.

The letters HPUS indicate that the components in this product are officially monographed in the Homeopathic
Pharmacopoeia of the United States.

Claims based on traditional homeopathic practice, not accepted medical evidence. Not FDA evaluated.

INDICATIONS AND USAGE

Indications: For dogs and cats with chronic joint problems, arthritis, and acute injury.

WARNINGS
FOR ANIMAL USE ONLY. KEEP OUT OF REACH OF CHILDREN. DO NOT USE IF TAMPER EVIDENT NECK SEAL IS BROKEN OR MISSING.

KEEP OUR OF REACH OF CHILDREN.

DOSAGE AND ADMINISTRATION

Directions: Add 4 pumps to a small amount of food twice per day for two weeks. After two weeks: Give once or twice per day as needed.
For more information or options to administer refer to our website.

INACTIVE INGREDIENT

Inactive Ingredients: Organic Ethanol 15%, Purified Water, Vegetable Non-GMO Glycerin.

Questions or Comments? 1-833-933-7839

Distributed by Adored Beast Apothecary

189 Business Park Rd, Eureka, Montana 59917

ADORED BEAST.COM

OTHER SAFETY INFORMATION

Safe use in pregnant animals or animals intended for breeding has not been proven.
If animal’s condition worsens or does not improve, discontinue use and consult your veterinarian.

PACKAGE LABEL

NDC#: 86083-0010-2

ADORED BEAST

APOTHECARY

JUMP FOR JOYNTS

Homeopathic

SUPPORTS HEALTHY JOINTS, BONES, LIGAMENTS, TENDONS, AND MUSCLE

For Cats & Dogs

PURPOSE

For dogs and cats with chronic joints problems, arthiritis, and acute injury.